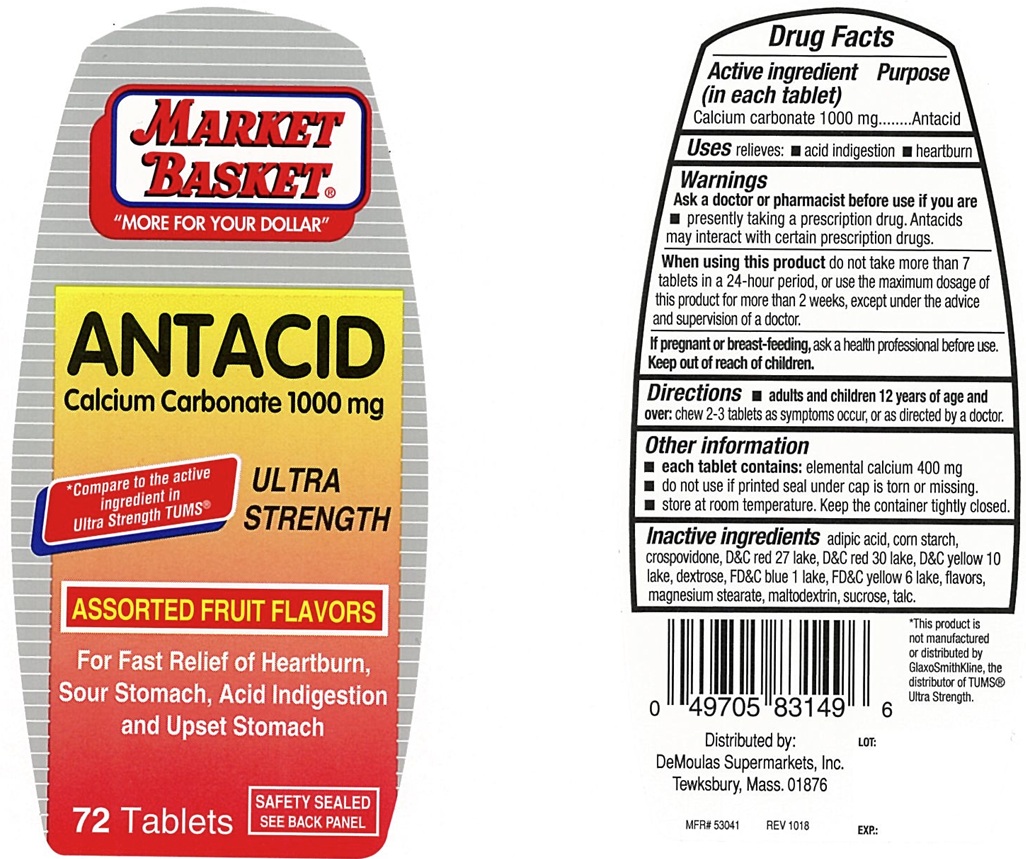 DRUG LABEL: Ultra Strength Antacid Assorted Fruit
NDC: 53942-171 | Form: TABLET, CHEWABLE
Manufacturer: DeMoulas Market Basket
Category: otc | Type: Human OTC Drug Label
Date: 20250305

ACTIVE INGREDIENTS: CALCIUM CARBONATE 1000 mg/1 1
INACTIVE INGREDIENTS: ADIPIC ACID; STARCH, CORN; CROSPOVIDONE, UNSPECIFIED; DEXTROSE, UNSPECIFIED FORM; FD&C BLUE NO. 1 ALUMINUM LAKE; MAGNESIUM STEARATE; MALTODEXTRIN; SUCROSE; TALC; D&C RED NO. 27 ALUMINUM LAKE; D&C RED NO. 30 ALUMINUM LAKE; D&C YELLOW NO. 10 ALUMINUM LAKE; FD&C YELLOW NO. 6 ALUMINUM LAKE

Ultra Strength Assorted Fruit Chewable Antacid

ACTIVE INGREDIENT (in each tablet)

Calcium carbonate 1000 mg

PURPOSE

Antacid

USE(S)

relieves:

- acid indigestion
- heartburn

WARNINGS

.

ASK A DOCTOR OR PHARMACIST BEFORE USE IF YOU ARE

- presently taking a prescription drug. Antacids may interact with certain prescription drugs.

WHEN USING THIS PRODUCT

do not take more than 7 tablets in a 24-hour period, or use the maximum dosage of this product for more than 2 weeks, except under the advice and supervision of a doctor.

IF PREGNANT OR BREASTFEEDING,

ask a health professional before use.

KEEP OUT OF REACH OF CHILDREN

.

DIRECTIONS

- adults and children 12 years of age and over: chew 2-3 tablets as symptoms occur, or as directed by a doctor.

OTHER INFORMATION

- each tablet contains: elemental calcium 400 mg
- do not use if printed seal under cap is torn or missing
- store at room temperature. keep the container tightly closed.

INACTIVE INGREDIENTS

adipic acid, corn starch, crospovidone, D&C red 27 lake, D&C red 30 lake, D&C yellow 10 lake, dextrose, FD&C blue 1 lake, FD&C yellow 6 lake, flavors, magnesium stearate, maltodextrin, sucrose, talc.

PRINCIPAL DISPLAY PANEL

MARKET BASKET

"MORE FOR YOUR DOLLAR"

ANTACID

ULTRA STRENGTH

Calcium Carbonate 1000 mg

*Compare to the active ingredient in TUMS®

ASSORTED FRUIT FLAVORS

72 Tablets